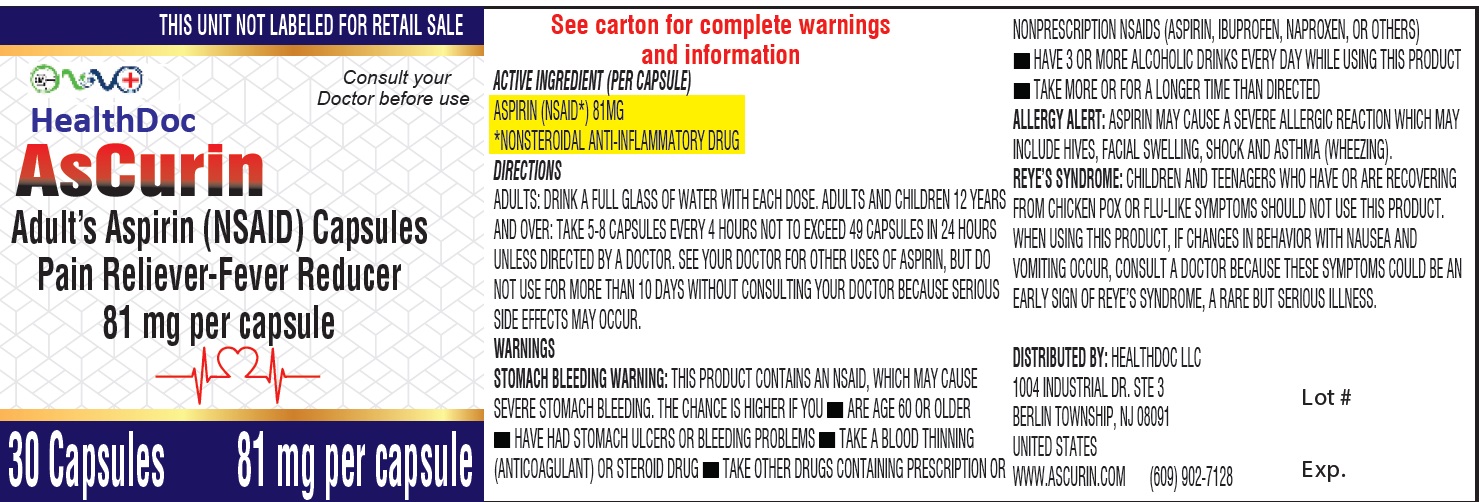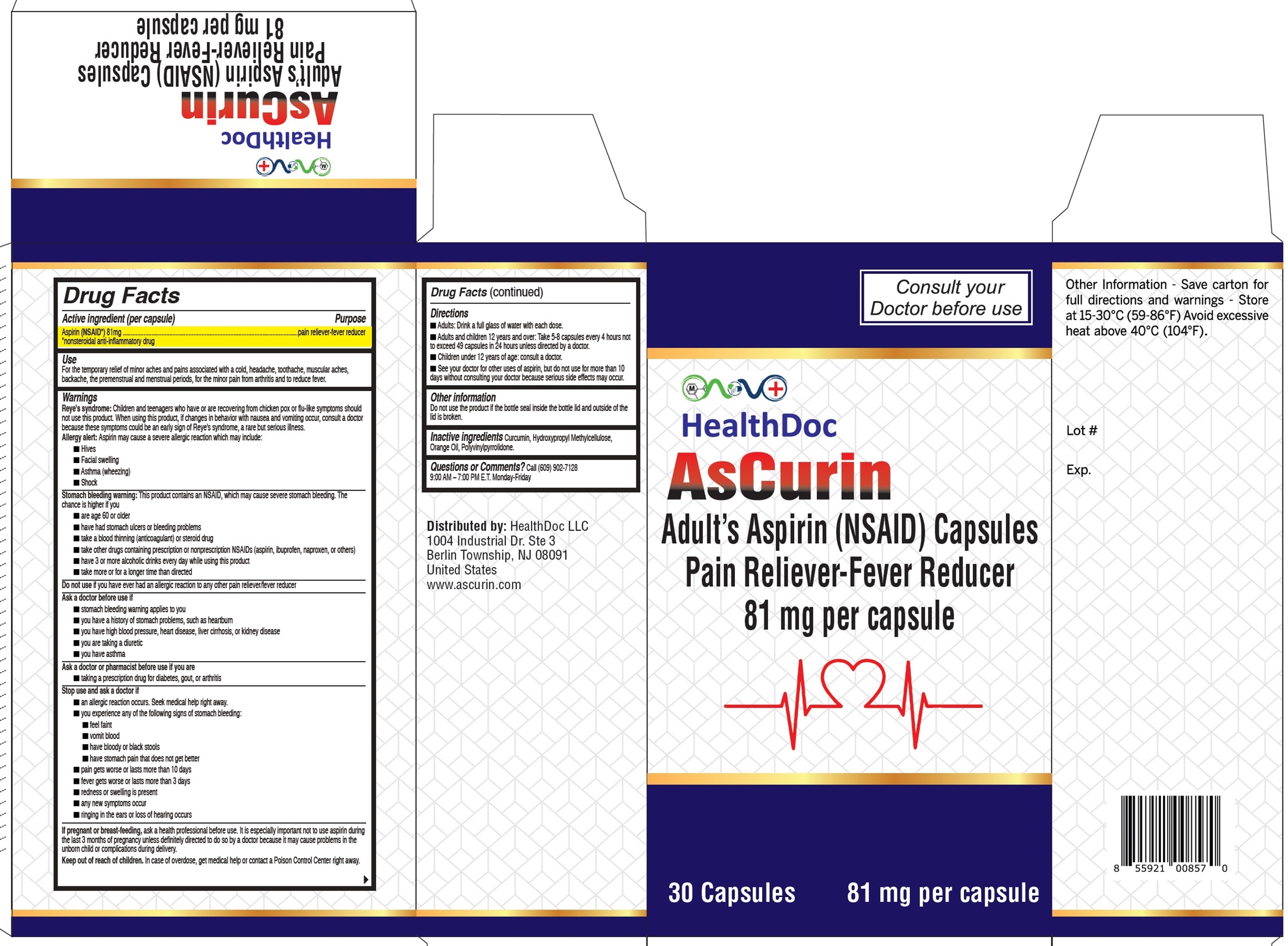 DRUG LABEL: Ascurin
NDC: 83607-002 | Form: CAPSULE
Manufacturer: Healthdoc LLC
Category: otc | Type: HUMAN OTC DRUG LABEL
Date: 20231113

ACTIVE INGREDIENTS: ASPIRIN 81 mg/1 1
INACTIVE INGREDIENTS: CURCUMIN; HYPROMELLOSE, UNSPECIFIED; ORANGE OIL, COLD PRESSED

Ascurin (Aspirin Capsules 81mg)

Active ingredient (per capsule)

Aspirin (NSAID*) 81mg

Purpose

pain reliever-fever reducer *nonsteriodal anti-inflammatory drug

Use

For the temporary relief of minor aches and pains associated with a cold, headache, toothache, muscular aches, backache, the premenstrual and menstrual periods, for the minor pain from arthritis and to reduce fever

Warnings

Reye's syndrome:Children and teenagers who have or are recovering from chicken pox or flu-like symptoms should not use this product. When using this product, if changes in behavior with nausea and vomiting occur, consult a doctor because these symptoms could be an early sign of Reye's syndrome, a rare but serious illness. Allergy alert: Aspirin may cause a severe allergic reaction which may include:

- Hives
- Facial swelling
- Asthma (wheezing)
- Shock

Stomach bleeding warning:This product contains an NSAID, which may cause severe stomach bleeding. The chance is higher if you

- are age 60 or older
- have had stomach ulcers or bleeding problems
- take a blood thinning (anticoagulant) or steroid drug
- take other drugs containing prescription or nonprescription NSAIDs (aspirin, ibuprofen, naproxen, or others)
- have 3 or more alcoholic drinks every day while using this product
- take more or for a longer time than directed

Do not use

if you have ever had an allergic reaction to any other pain reliever, fever reducer

Ask a doctor before use if

- stomach bleeding warning applies to you
- you have a history of stomach problems, such as heartburn
- you have high blood pressure, heart disease, liver cirrhosis, or kidney disease
- you are taking a diuretic
- you have asthma

Ask a doctor or pharmacist before use if you are

- taking a prescription drug for diabetes, gout, or arthritis

Stop use and ask a doctor if

- an allergic reaction occurs. Seek medical help right away.
- you experience any of the following signs of stomach bleeding:
- feel faint
- vomit blood
- have bloody or black stools
- have stomach pain that does not get better
- pain gets worse or lasts more than 10 days
- fever gets worse or lasts more than 3 days
- redness or swelling is present
- any new symptoms occur
- ringing in the ears or loss of hearing occurs

If pregnant or breast-feeding,

ask a health professional before use. It is especially important not to use aspirin during the last 3 months of pregnancy unless definitely directed to do so by a doctor because it may cause problems in the unborn child or complications during delivery.

Keep out of reach of children.

In case of overdose, get medical help or contact a Poison Control Center right away.

Directions

- Adults: Drink a full glass of water with each dose.
- Adults and children 12 years and over: Take 5-8 capsules every 4 hours not to exceed 49 capsules in 24 hours unless directed by a doctor.
- Children under 12 years of age: consult a doctor.
- See your doctor for other uses of aspirin, but do not use for more than 10 days without consulting your doctor because serious side effects may occur.

Other information

Do not use the product if the bottle seal inside the bottle lid is broken.

Inactive ingredients

Curcumin, Hydroxypropyl Methylcellulose, Orange Oil, Polyvinylpyrrolidone.

Questions or Comments?

Call (609) 902-7128 9:00 AM – 7:00 PM E.T. Monday-Friday